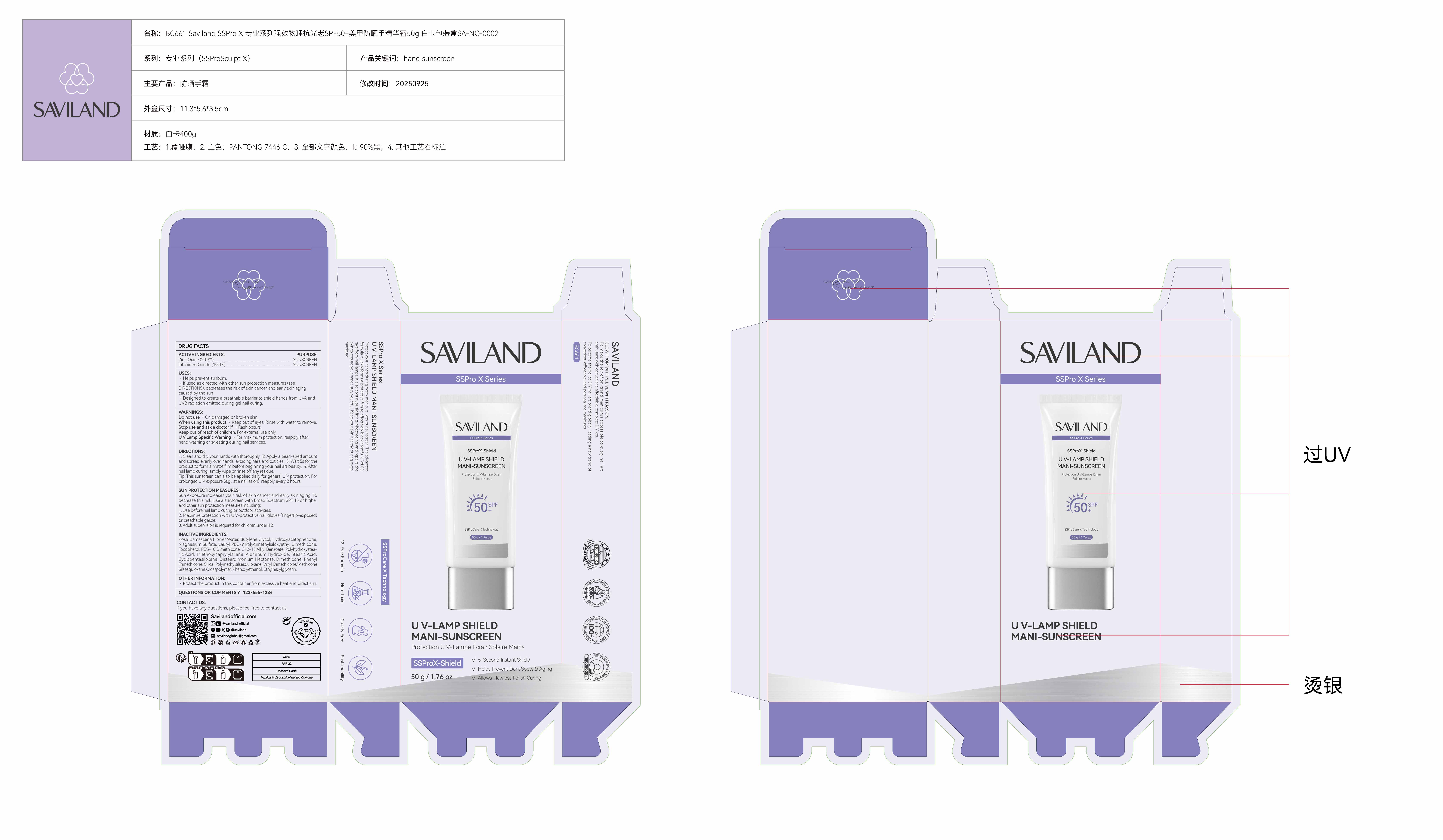 DRUG LABEL: U V-Lamp Shield Mani-Sunscreen
NDC: 85966-004 | Form: LIQUID
Manufacturer: GUANGZHOU SAWEILAN IMPORT & EXPORT TRADING CO., LTD
Category: otc | Type: HUMAN OTC DRUG LABEL
Date: 20250928

ACTIVE INGREDIENTS: TITANIUM DIOXIDE 5 g/50 g; ZINC OXIDE 10.15 g/50 g
INACTIVE INGREDIENTS: ETHYLHEXYLGLYCERIN; HYDROXYACETOPHENONE; C12-15 ALKYL BENZOATE; ALUMINUM HYDROXIDE; CYCLOPENTASILOXANE; POLYMETHYLSILSESQUIOXANE/TRIMETHYLSILOXYSILICATE; TOCOPHEROL; PHENYL TRIMETHICONE; VINYL DIMETHICONE/METHICONE SILSESQUIOXANE CROSSPOLYMER; PHENOXYETHANOL; PEG-10 DIMETHICONE (220 CST); STEARIC ACID; SILICA; TRIETHOXYCAPRYLYLSILANE; BUTYLENE GLYCOL; DIMETHICONE; MAGNESIUM SULFATE; LAURYL PEG-9 POLYDIMETHYLSILOXYETHYL DIMETHICONE; DISTEARDIMONIUM HECTORITE; POLYHYDROXYSTEARIC ACID (2300 MW); ROSA DAMASCENA FLOWER OIL

85966-004 U V-Lamp Shield Mani-Sunscreen

ACTIVE INGREDIENT

ZINC OXIDE 20.3%
TITANIUM DIOXIDE 10%

PURPOSE

SUNSCREEN

INDICATIONS AND USAGE

Helps prevent sunburn.
lf used as directed with other sun protection measures (see DIRECTIONS), decreases the risk of skin cancer and early skin agingcaused by the sun
Desiqned to create a breathable barrier to shield hands from UVA and UVB radiation emitted during gel nail curing.

Do not use ·On damaged or broken skin.
When using this product · Keep out of eyes. Rinse with water to remove.
Stop use and ask a doctor if · Rash occurs.
Keep out of reach of children. For external use only.
UV Lamp Specific Warning ·For maximum protection, reapply after hand washing or sweating during nail services.

Do not use ·On damaged or broken skin.

When using this product · Keep out of eyes. Rinse with water to remove.

Stop use and ask a doctor if · Rash occurs.

Keep out of reach of children.

DOSAGE AND ADMINISTRATION

1. Clean and dry your hands with thoroughly.
2. Apply a pearl-sized amountand spread evenly over hands, avoiding nails and cuticles.
3. Wait 5s for theproduct to form a matte film before beginning your nail art beauty.
4. Afternail lamp curing, simply wipe or rinse off any residue.
Tip: This sunscreen can also be applied daily for general U V protection. Forprolonged UV exposure (e.g., at a nail salon), reapply every 2 hours.

INACTIVE INGREDIENT

ROSA DAMASCENA FLOWER WATER
BUTYLENE GLYCOL
HYDROXYACETOPHENONE
MAGNESIUM SULFATE
LAURYL PEG-9 POLYDIMETHYLSILOXYETHYL DIMETHICONE
TOCOPHEROL
PEG-10 DIMETHICONE
C12-15 ALKYL BENZOATE
POLYHYDROXYSTEARIC ACID
TRIETHOXYCAPRYLYLSILANE
ALUMINUM HYDROXIDE
STEARIC ACID
CYCLOPENTASILOXANE
DISTEARDIMONIUM HECTORITE
DIMETHICONE
PHENYL TRIMETHICONE
SILICA
POLYMETHYLSILSESQUIOXANE
VINYL DIMETHICONE/METHICONE SILSESQUIOXANE CROSSPOLYMER
PHENOXYETHANOL
ETHYLHEXYLGLYCERIN